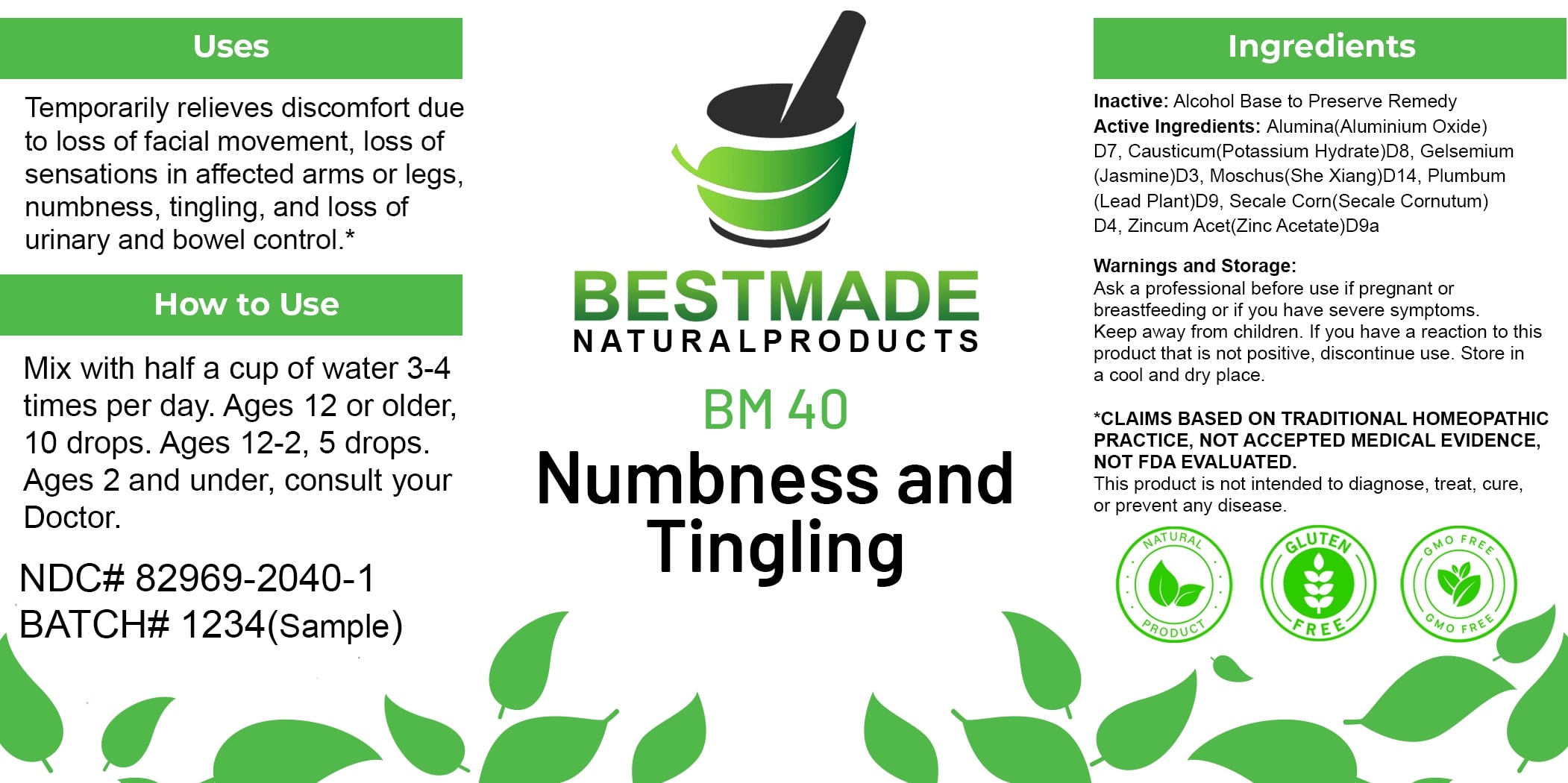 DRUG LABEL: Bestmade Natural Products BM40
NDC: 82969-2040 | Form: LIQUID
Manufacturer: Bestmade Natural Products
Category: homeopathic | Type: HUMAN OTC DRUG LABEL
Date: 20250123

ACTIVE INGREDIENTS: MOSCHUS MOSCHIFERUS MUSK SAC RESIN 30 [hp_C]/30 [hp_C]; ZINC ACETATE 30 [hp_C]/30 [hp_C]; LEAD 30 [hp_C]/30 [hp_C]; CLAVICEPS PURPUREA SCLEROTIUM 30 [hp_C]/30 [hp_C]; ALUMINUM OXIDE 30 [hp_C]/30 [hp_C]; CAUSTICUM 30 [hp_C]/30 [hp_C]; GELSEMIUM SEMPERVIRENS ROOT 30 [hp_C]/30 [hp_C]
INACTIVE INGREDIENTS: ALCOHOL 30 [hp_C]/30 [hp_C]

BM40

DOSAGE AND ADMINISTRATION

How to Use

Mix with half a cup of water 3-4 times per day. Ages 12 or older, 10 drops. Ages 12-2, 5 drops. Ages 2 and under, consult your Doctor.

Uses

Temporarily relieves discomfort due to loss of facial movement, loss of sensations in affected arms or legs, numbness, tingling, and loss of urinary and bowel control.*

*CLAIMS BASED ON TRADITIONAL HOMEOPATHIC PRACTICE, NOT ACCEPTED MEDICAL EVIDENCE, NOT FDA EVALUATED.

This product is not intended to diagnose, treat, cure, or prevent any disease.

Uses

Temporarily relieves discomfort due to loss of facial movement, loss of sensations in affected arms or legs, numbness, tingling, and loss of urinary and bowel control.*

*CLAIMS BASED ON TRADITIONAL HOMEOPATHIC PRACTICE, NOT ACCEPTED MEDICAL EVIDENCE, NOT FDA EVALUATED.

This product is not intended to diagnose, treat, cure, or prevent any disease.

INACTIVE INGREDIENT

Ingredients

Inactive: Alcohol Base to Preserve Remedy

ACTIVE INGREDIENT

Active Ingredients: Alumina(Aluminium Oxide) D7, Causticum (Potassium Hydrate)D8, Gelsemium (Jasmine)D3, Moschus(She Xiang)D14, Plumbum (Lead Plant)D9, Secale Corn (Secale Cornutum) D4, Zincum Acet (Zinc Acetate)D9a

KEEP OUT OF REACH OF CHILDREN

Warnings and Storage:

Ask a professional before use if pregnant or breastfeeding or if you have severe symptoms. Keep away from children. If you have a reaction to this product that is not positive, discontinue use. Store in a cool and dry place.

Warnings and Storage:

Ask a professional before use if pregnant or breastfeeding or if you have severe symptoms. Keep away from children. If you have a reaction to this product that is not positive, discontinue use. Store in a cool and dry place.

*CLAIMS BASED ON TRADITIONAL HOMEOPATHIC PRACTICE, NOT ACCEPTED MEDICAL EVIDENCE, NOT FDA EVALUATED.

This product is not intended to diagnose, treat, cure, or prevent any disease.

Entire package label